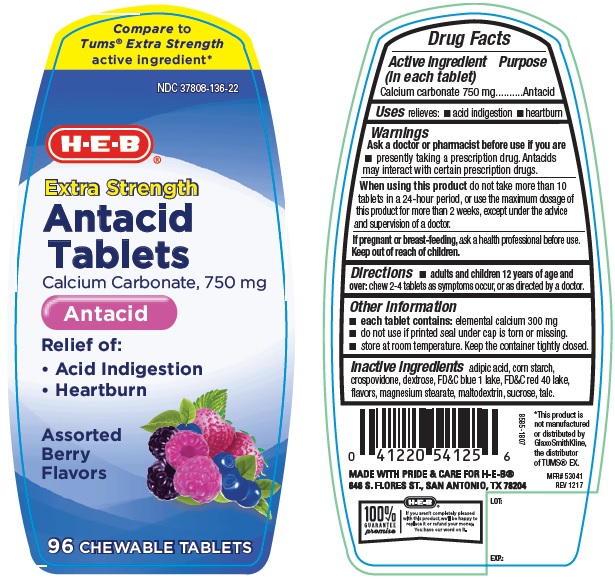 DRUG LABEL: HEB Extra Stregth Antacid
NDC: 37808-136 | Form: TABLET, CHEWABLE
Manufacturer: H E B
Category: otc | Type: Human OTC Drug Label
Date: 20250120

ACTIVE INGREDIENTS: CALCIUM CARBONATE 750 mg/1 1
INACTIVE INGREDIENTS: ADIPIC ACID; STARCH, CORN; CROSPOVIDONE, UNSPECIFIED; DEXTROSE, UNSPECIFIED FORM; FD&C BLUE NO. 1; FD&C RED NO. 40; MAGNESIUM STEARATE; MALTODEXTRIN; SUCROSE; TALC

HEB Extra Strength Antacid Assorted Berry Chewable Tablets

ACTIVE INGREDIENT (in each tablet)

Calcium carbonate 750 mg

PURPOSE

Antacid

USE(S)

relieves:

- acid indigestion
- heartburn

WARNINGS

.

ASK A DOCTOR OR PHARMACIST BEFORE USE IF YOU ARE

- presently taking a prescription drug. Antacids may interact with certain prescription drugs.

WHEN USING THIS PRODUCT

do not take more than 10 tablets in a 24-hour period, or use the maximum dosage of this product for more than 2 weeks, except under the advice and supervision of a doctor.

IF PREGNANT OR/BREASTFEEDING,

ask a health professional before use.

KEEP OUT OF REACH OF CHILDREN

.

DIRECTIONS

- adults and children 12 years of age and over: chew 2-4 tablets as symptoms occur, or as directed by a doctor.

OTHER INFORMATION

- each tablet contains: elemental calcium 300 mg
- do not use if printed seal under the cap is torn or missing
- store at room temperature. keep the container tightly closed.

INACTIVE INGREDIENTS

adipic acid, corn starch, crospovidone, dextrose, FD&C blue 1 lake, FD&C red 40 lake, flavors, magnesium stearate, maltodextrin, sucrose, talc.

PRINCIPAL DISPLAY PANEL

Compare to Tums® Extra Strength active ingredient*
NDC 37808-136-22
H E B
Extra Strength
Antacid
Tablets
Calcium Carbonate 750 mg
Antacid
Relief of :

- Acid Indigestion
- Heartburn

Assorted Berry Flavors
96 CHEWABLE TABLETS